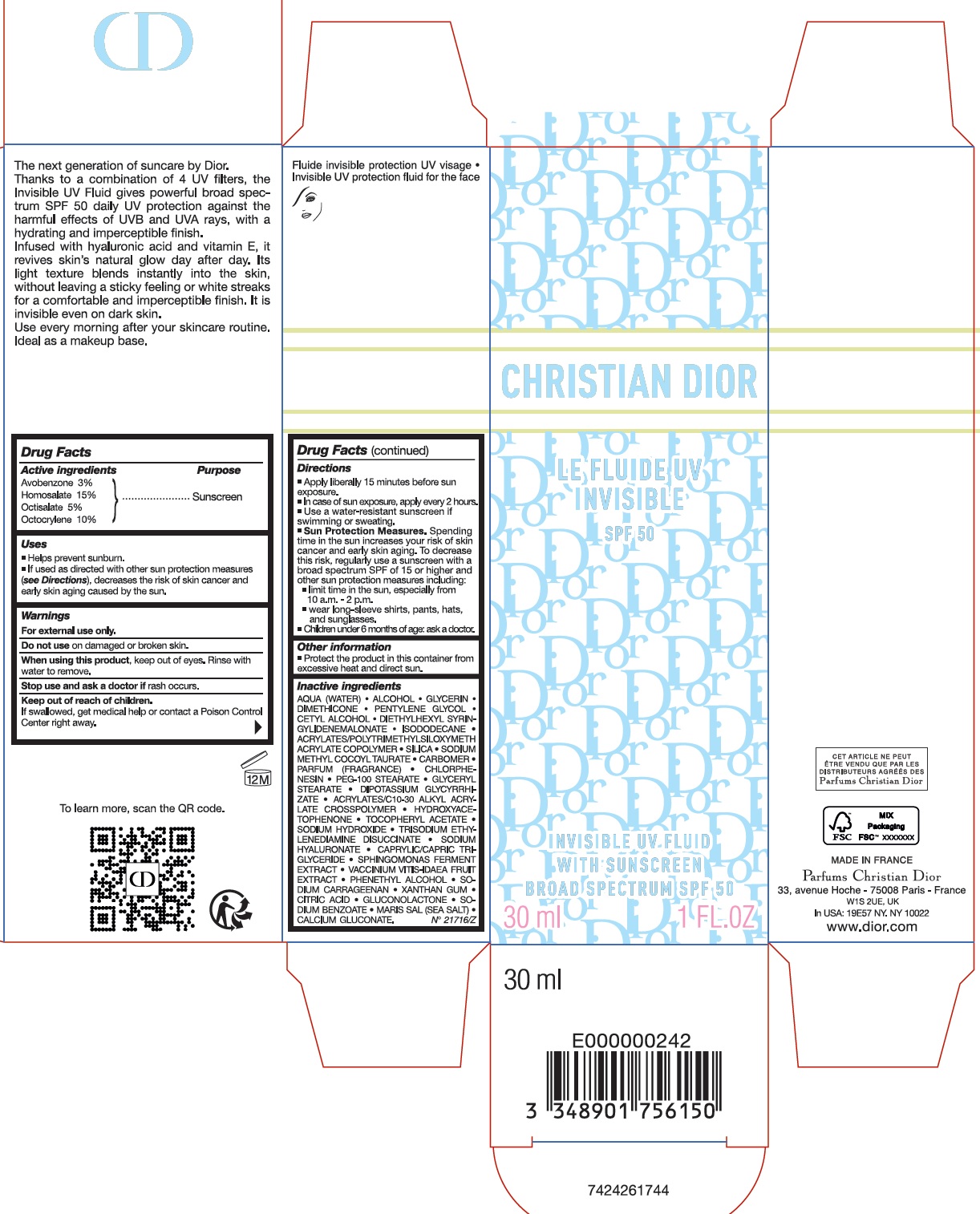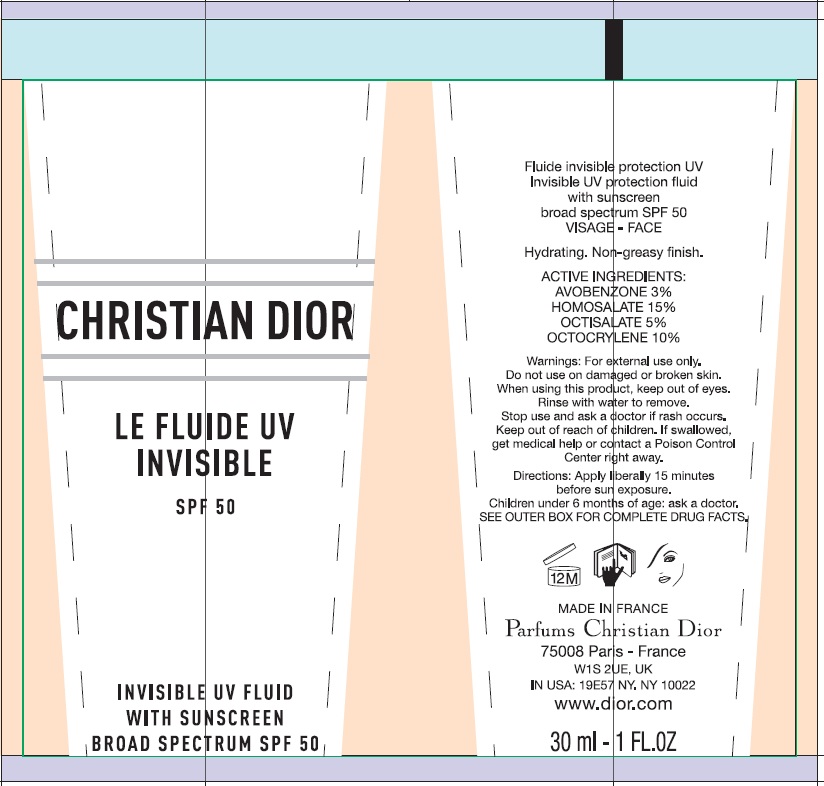 DRUG LABEL: Christian Dior Invisible UV Fluid with Sunscreen Broad Spectrum SPF 50
NDC: 61957-3600 | Form: EMULSION
Manufacturer: Parfums Christian Dior
Category: otc | Type: HUMAN OTC DRUG LABEL
Date: 20260120

ACTIVE INGREDIENTS: AVOBENZONE 30 mg/1 mL; HOMOSALATE 150 mg/1 mL; OCTISALATE 50 mg/1 mL; OCTOCRYLENE 100 mg/1 mL
INACTIVE INGREDIENTS: WATER; ALCOHOL; GLYCERIN; DIMETHICONE; PENTYLENE GLYCOL; CETYL ALCOHOL; DIETHYLHEXYL SYRINGYLIDENEMALONATE; ISODODECANE; SILICON DIOXIDE; SODIUM METHYL COCOYL TAURATE; CARBOMER HOMOPOLYMER, UNSPECIFIED TYPE; HYDROXYACETOPHENONE; .ALPHA.-TOCOPHEROL ACETATE; SODIUM HYDROXIDE; TRISODIUM ETHYLENEDIAMINE DISUCCINATE; SODIUM HYALURONATE; MEDIUM-CHAIN TRIGLYCERIDES; LINGONBERRY; PHENYLETHYL ALCOHOL; SODIUM CARRAGEENAN; XANTHAN GUM; CITRIC ACID MONOHYDRATE; GLUCONOLACTONE; SODIUM BENZOATE; SEA SALT; CALCIUM GLUCONATE

Christian Dior Invisible UV Fluid with Sunscreen Broad Spectrum SPF 50

Active ingredients

Avobenzone 3%
Homosalate 15%
Octisalate 5%
Octocrylene 10%

Purpose

Sunscreen

Uses

- Helps prevent sunburn.
- If used as directed with other sun protection measures (see Directions), decreases the risk of skin cancer and early skin aging caused by the sun.

Warnings

For external use only.

Do not use

on damaged or broken skin.

When using this product,

keep out of eyes. Rinse with water to remove.

Stop use and ask a doctor if

rash occurs.

Keep out of reach of children.

If swallowed, get medical help or contact a Poison Control Center right away.

Directions

- Apply liberally 15 minutes before sun exposure.
- In case of sun exposure, apply every 2 hours.
- Use a water-resistant sunscreen if swimming or sweating.
- Sun Protection Measures.Spending time in the sun increases your risk of skin cancer and early skin aging. To decrease this risk, regularly use a sunscreen with a broad spectrum SPF of 15 or higher and other sun protection measures including:
- limit time in the sun, especially from 10 a.m. - 2 p.m.
- wear long-sleeve shirts, pants, hats, and sunglasses.
- Children under 6 months of age: ask a doctor.

Other information

- Protect the product in this container from excessive heat and direct sun.

Inactive ingredients

AQUA (WATER) • ALCOHOL • GLYCERIN • DIMETHICONE • PENTYLENE GLYCOL • CETYL ALCOHOL • DIETHYLHEXYL SYRINGYLDENEMALONATE • ISODODECANE • ACRYLATES/POLYTRIMETHYLSILOXYMETH ACRYLATES COPOLYMER • SILICA • SODIUM METHYL COCOYL TAURATE • CARBOMER • PARFUM (FRAGRANCE) • CHLORRHIZATE • ACRYLATES/ C10-30 ALKYL ACRYLATE CROSSPOLYMER • HYDROXYACETOPHENONE • TOCOPHERYL ACETATE • SODIUM HYDROXIDE • TRISODIUM ETHYLENEDIAMINE DISUCCINATE • SODIUM HYALURONATE • CAPRYLIC/CAPRIC TRIGLYCERIDE • SPHINGOMONAS FERMENT EXTRACT • VACCINIUM VITIS-IDAEA FRUIT EXTRACT • PHENETHYL ALCOHOL • SODIUM CARRAGEENAN • XANTHAN GUM • CITRIC ACID • GLUCONOLACTONE • SODIUM BENZOATE • MARIS SAL (SEA SALT) • CALCIUM GLUCONATE. N° 21716/Z